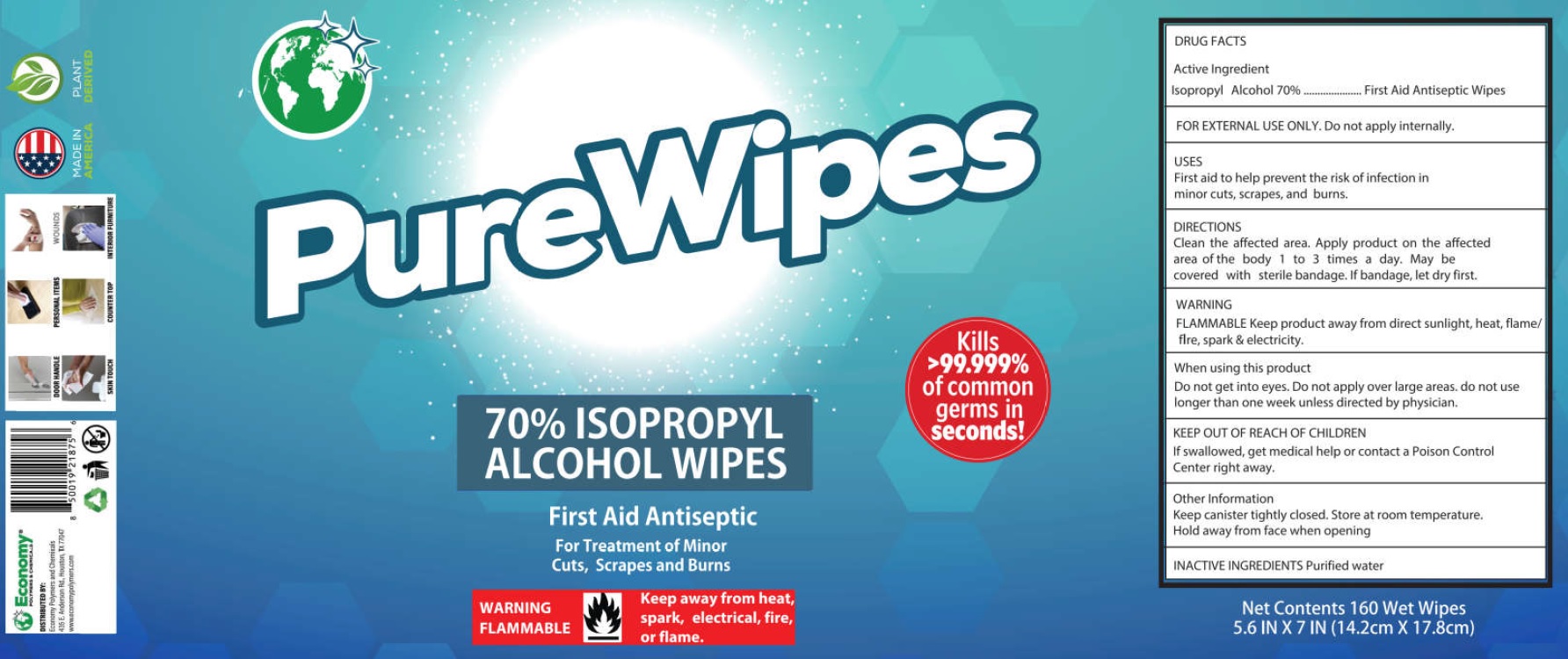 DRUG LABEL: Pure Wipes 70 Alcohol Wipes
NDC: 74830-003 | Form: CLOTH
Manufacturer: Economy Polymers and Chemicals
Category: otc | Type: HUMAN OTC DRUG LABEL
Date: 20210305

ACTIVE INGREDIENTS: ISOPROPYL ALCOHOL 70 mL/100 mL
INACTIVE INGREDIENTS: WATER

Pure Wipes 70% Alcohol Wipes

Active Ingredient

Isopropyl Alcohol 70%

Purpose

First Aid Antiseptic Wipes

USES

First aid to help prevent the risk of infection in minor cuts, scrapes, and burn.

DIRECTIONS

Clean the affected area. Apply product on the affected area of the body 1 to 3 times a day. May be covered with sterile bandgae. If bandage, let dry first.

WARNING

FOR EXTERNAL USE ONLY. Do not apply internally.

FLAMMABLE Keep product away from direct sunlight, heat, flame/fire, spark & electricity.

When using this product

Do not get into eyes. Do not apply over large areas. do not use longer than one week unless directed by physician.

KEEP OUT OF REACH OF CHILDREN

If swallowed, get medical help or contact a Poison Control Center right away.

Other Information

Keep canister tightly closed. Store at room temperature. Hold away from face when opening

INACTIVE INGREDIENT

Purified water